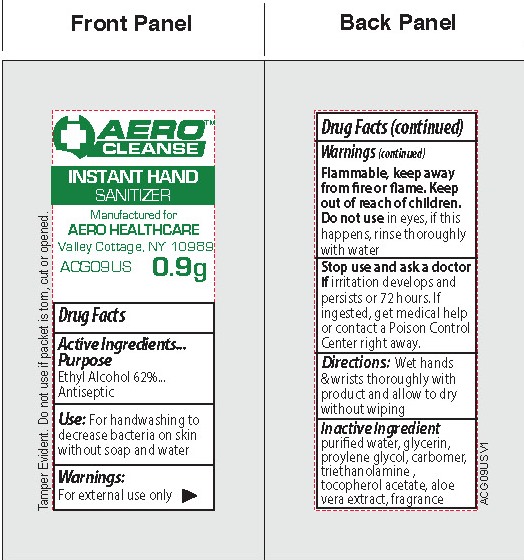 DRUG LABEL: AEROCLEANSE Instant Hand Sanitizer
NDC: 55305-124 | Form: GEL
Manufacturer: Aero Healthcare
Category: otc | Type: HUMAN OTC DRUG LABEL
Date: 20250312

ACTIVE INGREDIENTS: ALCOHOL 62 g/100 g
INACTIVE INGREDIENTS: WATER; PROPYLENE GLYCOL; ALOE VERA LEAF; GLYCERIN

Aerocleanse Instant Hand Sanitizer 0.9g

Active Ingredients

Ethyl Alcohol 62%

Purpose

Antiseptic

Use

For handwashing to decrease bacteria on skin without soap and water

Warnings

For External Use Only

Flammable, keep away from fire or flame.

Do not use:

in eyes. If this happens, rinse thoroughly with water.

Stop use and ask a doctor if

irritation develops and persists for 72 hours. If ingested, get medical help or contact a Poison Control Center right away.

Directions

Wet hands & wrists thoroughly with product and allow to dry without wiping.

Inactive Ingredients

purified water, glycerin, proylene glycol, carbomer, triethanolamine, tocopherol acetate, aloe vera extract, fragrance

Package Label

Aerocleanse

Instant Hand Sanitizer

Manufactured for

Aero Healthcare

Valley Cottage, NY 10989

ACG09US 0.9g